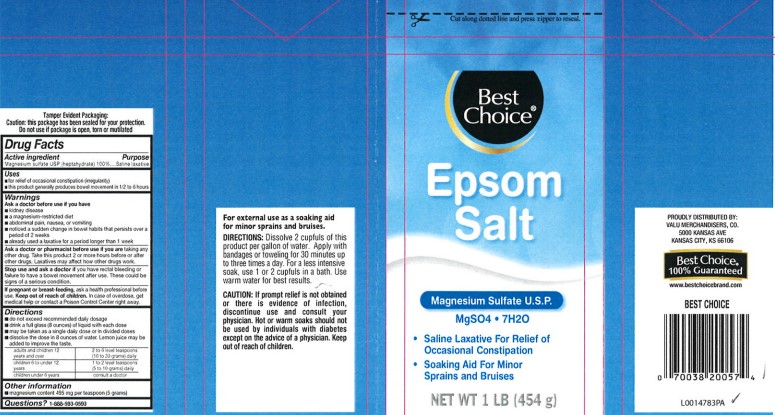 DRUG LABEL: Epsom Salt
NDC: 63941-602 | Form: GRANULE, FOR SOLUTION
Manufacturer: Valu Merchandisers Company
Category: otc | Type: HUMAN OTC DRUG LABEL
Date: 20260216

ACTIVE INGREDIENTS: MAGNESIUM SULFATE HEPTAHYDRATE 1 g/1 g

Best Choice 602.002/602AA
Epsom Salt

Tamper Evident Statement

Tamper Evident Packaging:

Caution: this package has been sealed for your protection.

Do not use if package is open, torn or mutiltated.

Active ingredient

Magnesium sulfate USP (heptahydrate) 100%

Purpose

Saline Laxative

Use

- for relief of occasional constipation (irregularity)
- this product generally produces bowel movement in 1/2 to 6 hours

Warnings

for this product

Ask a doctor before use if you have

- kidney disease
- a magnesium-restricted diet
- abdominal pain, nausea, or vomiting
- noticed a sudden change in bowel habits that persists over a period of 2 weeks
- already used a laxative for a period longer than 1 week

Ask a doctor or pharmacist before use if you are

taking any other drug. Take this product 2 or more hours before or after other drugs. Laxatives may affect how other drugs work.

Stop use and ask a doctor if

you have rectal bleeding or failure to have a bowel movement after use. These could be signs of a serious condition.

If pregnant or breast-feeding,

ask a health professional before use.

Keep out of reach of children.

In case of overdose, get medical help or contact a Poison Control Center right away.

Directions

- do not exceed recommended daily dosage
- drink a full glass (8 ounces) of liquid with each dose
- may be taken as a single daily dose or in divided doses
- dissolve the dose in 8 ounces of water. Lemon juice may be added to improve the taste

adults and children 12 years and over - 2 to 6 level teaspoons (10 to 30 grams) daily

children 6 to under 12 years - 1 to 2 level teaspoons (5 to 10 grams) daily

children under 6 years - consult a doctor

Inactive Ingredient

None

Other information

- magnesium content 495 mg per teaspoon (5 grams)

Questions?

1-888-593-0593

Claims

For external use as a soaking aid for minor sprains and bruises.

DIRECTIONS:Dissolve 2 cupfuls of this product per gallon of water. Apply with bandages or toweling for 30 minutes up to three times a day. For less intensive soak, use 1 or 2 cupfuls in a bath. Use warm water for best results.

CAUTION: If prompt relief is not obtained or there is evidence of infection, discontinue use and consult your physician. Hot or warm soaks should not be used by individuals with diabetes except on the advice of a phsician. Keep out of reach of children.

ADVERSE REACTION

Proudly Distributed By:

Valu Merchandisers, Co.

5000 Kansas Ave

Kansas City, KS 66106

Best Choice®

100% Guaranteed

www.bestchoicebrand.com

BEST CHOICE

principal display panel

Cut along dotted line and press zipper to reseal.

Best Choice®

Epsom Salt

Magnesium Sulfate U.S.P.

MgSO4• 7H2O

- Saline Laxative For relief of Occasional Constipation
- Soaking Aid For Minor Sprains and Bruises

NET WT 1 LB (454 g)